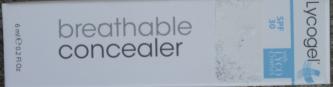 DRUG LABEL: Lycogel Cover and Recovery - Breathable Concealer - SPF 30 with LYCO Complex
NDC: 62742-4032 | Form: CREAM
Manufacturer: Allure Cosmetic, Inc.
Category: otc | Type: HUMAN OTC DRUG LABEL
Date: 20100208

ACTIVE INGREDIENTS: TITANIUM DIOXIDE 65 mg/1 mL; ZINC OXIDE 82 mg/1 mL
INACTIVE INGREDIENTS: WATER; CYCLOMETHICONE 5; DIMETHICONE; CYCLOMETHICONE; APPLE; CYPERUS ROTUNDUS ROOT; XANTHIUM; HYALURONATE SODIUM; SQUALANE; VITAMIN A PALMITATE; .ALPHA.-TOCOPHEROL ACETATE, D-; ASCORBYL PALMITATE; BETA CAROTENE; PHELLODENDRON AMURENSE; BARLEY; CENTELLA ASIATICA; XANTHAN GUM; GLYCERIN; LECITHIN, SOYBEAN; MANNITOL; SODIUM CITRATE; ALUMINUM HYDROXIDE; STEARIC ACID; PHENOXYETHANOL; CAPRYLYL GLYCOL; ETHYLHEXYLGLYCERIN; HEXYLENE GLYCOL; SODIUM BENZOATE

Drug Facts

Active Ingredients: 6.5% TITANIUM DIOXIDE

8.2% ZINC OXIDE

Inactive Ingredients:
WATER, CYCLOPENTASILOXANE, DIMETHICONE, PEG-10/15 CROSSPOLYMER, CYCLOMETHICONE, SACCHAROMYCES LYSATE EXTRACT, HYDRATED SILICA, PEG/PPG-18/18 DIMETHICONE, MALUS DOMESTICA FRUIT CELL CULTURE, CYPERUS ROTUNDUS ROOT EXTRACT, LONICERA JAPONICA FLOWER EXTRACT, XANTHIUM SIBIRICUM FRUIT EXTRACT, SODIUM HYALURONATE, SQUALANE (OLIVE), ACETYL TETRAPEPTIDE-15, PHOSPHOLIPIDS, RETINYL PALMITATE, TOCOPHEROL ACETATE, ASCORBYL PALMITATE, BETA-CAROTENE, SANTALUM ALBUM (SANDALWOOD) EXTRACT, PHELLODENDRON AMURENSE BARK EXTRACT, HORDEUM DISTICHON (BARLEY) EXTRACT, OLEA EUROPAEA (OLIVE) LEAF EXTRACT, ALGAE EXTRACT, ARTEMISIA VULGARIS EXTRACT, ZINC PCA, CENTELLA ASIATICA EXTRACT, POLYGLYCERYL-3 POLYDIMETHYLSILOXYETHYL DIMETHICONE, ACRYLATES ETHYLHEXYL ACRYLATE, TRIETHOXYSILYLETHYL POLYDIMETHYLSILOXYETHYL HEXYL DIMETHICONE, XANTHAN GUM, GLYCERIN, LECITHIN, MANNITOL, SODIUM CITRATE, ALUMINUM HYDROXIDE, STEARIC ACID, PHENOXYETHANOL, ISOHEXADECANE, CAPRYLYL GLYCOL, ETHYLHEXYLGYCERINE, HEXYLENE GLYCOL, SODIUM BENZOATE.
MAY CONTAIN: Cl 77491, Cl 77492, Cl 77499 (IRON OXIDE), Cl 77891 (TITANIUM DIOXIDE)

Information on Carton Label:

1. Principal Display Panel: Shown in the image below.

2. Back Panel:

Manufactured for and distributed by

Quura Medical, BV. 1272 CB, The Netherlands

www.lycogel.eu

-------------------------------------------

Active Ingredients:

Inactive Ingredients:

(as listed above)

3. Side Panel A: Lycogel Cover and Recovery

4. Side Panel B: Use Benefits

The first breathable colour corrective treatment that combines cosmetic and skincare technology to promote post procedure healing, soothe sensitive skin, rejuvenate and camouflage at the same time.

Lycogel's revolutionary technology combines a unique breathable Tripple Silica Gel Base with LYCO Complex, a carefully balanced set of bio-active agents that work synergistically to improve the skin.

Directions: Dispense a small amount and apply with clean sponge or fingertips. Apply in buildable layers for more coverage using a patting technique.

Warning: For external use only. Avoid contact with eyes. Discontinue use if irritation occurs and consult your skin specialist.

5.Top: Cover and Recovery printed in white on gray background.

6. Bottom: Shade name sticker (Green, Pink, Oaker, and Yellow)